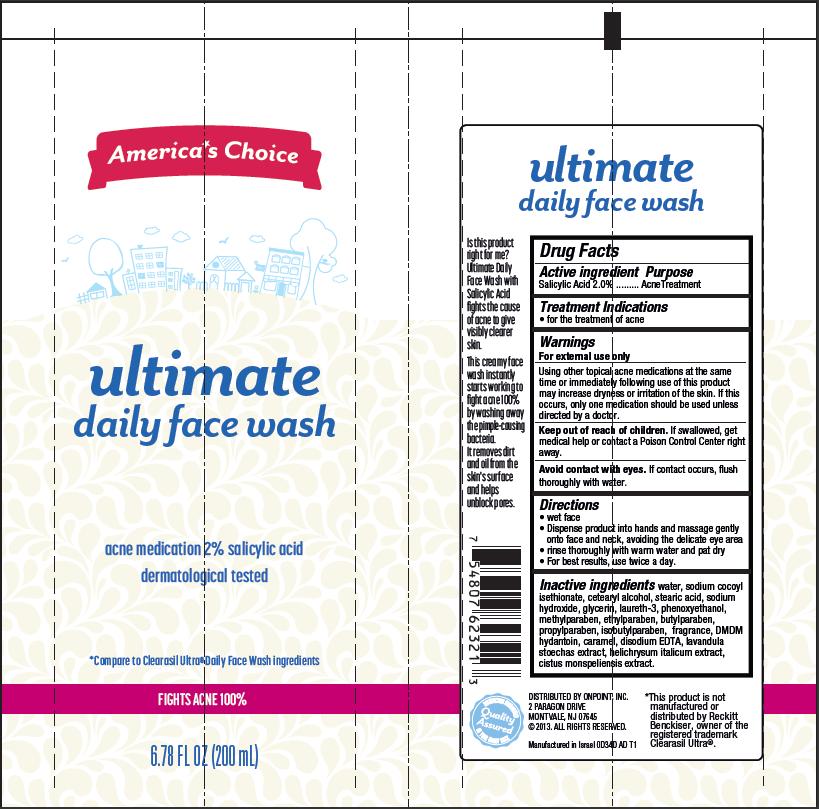 DRUG LABEL: Ultimate Daily Face Wash
NDC: 42421-034 | Form: CREAM
Manufacturer: Emilia Personal Care Inc.
Category: otc | Type: HUMAN OTC DRUG LABEL
Date: 20140109

ACTIVE INGREDIENTS: SALICYLIC ACID 2 g/100 mL
INACTIVE INGREDIENTS: WATER; SODIUM COCOYL ISETHIONATE; CETOSTEARYL ALCOHOL; STEARIC ACID; SODIUM HYDROXIDE; GLYCERIN; LAURETH-3; PHENOXYETHANOL; METHYLPARABEN; ETHYLPARABEN; BUTYLPARABEN; PROPYLPARABEN; ISOBUTYLPARABEN; DMDM HYDANTOIN; CARAMEL; EDETATE DISODIUM; LAVANDULA STOECHAS FLOWERING TOP; HELICHRYSUM ITALICUM FLOWER; CISTUS MONSPELIENSIS LEAF

America's Choice ultimate daily face wash

Active ingredient

Salicylic Acid 2.0%

Purpose

Acne Treatment

Treatment Indications

- for the treatment of acne

Warnings

For external use only.

Using other topical acne medications at the same time or immediately following use of this product may increase dryness or irritation of the skin. If this occurs, only one medication should be used unless directed by a doctor.

Keep Out of Reach of Children.

If swallowed, get medical help or contact a Poison Control Center right away.

Avoid contact with eyes.

If contact occurs, flush thoroughly with water.

Directions

- wet face
- Dispense product into hands and massage gently onto face and neck, avoiding the delicate eye area
- rinse thoroughly with warm water and pat dry
- For best results, use twice a day.

Inactive Ingredients

water, sodium cocoyl isethionate, cetearyl alcohol, stearic acid, sodium hydroxide, glycerin, laureth-3, phenoxyethanol, methylparaben, ethylparaben, butylparaben, propylparaben, isobutylparaben, fragrance, DMDM hydantoin, caramel, disodium EDTA, lavandula stoechas extract, helichrysum italicum extract, cistus monspeliensis extract.

Package/Label Principal Display Panel

America's Choice

ultimate daily face wash
acne medication 2% salicylic acid

dermatological tested

*Compare to Clearasil Ultra®
Daily Face Wash ingredients

FIGHTS ACNE 100%

6.78 FL OZ (200 mL)

*This product is not manufactured or distributed by Reckitt Benckiser, owner of the registered trademark Clearasil Ultra®.

DISTRIBUTED BY ONPOINT INC.:
2 PARAGON DRIVE
MONTVALE, NJ 07645
©2013. ALL RIGHTS RESERVED.
Manufactured in Israel 0D34D AD T1

Carton Label